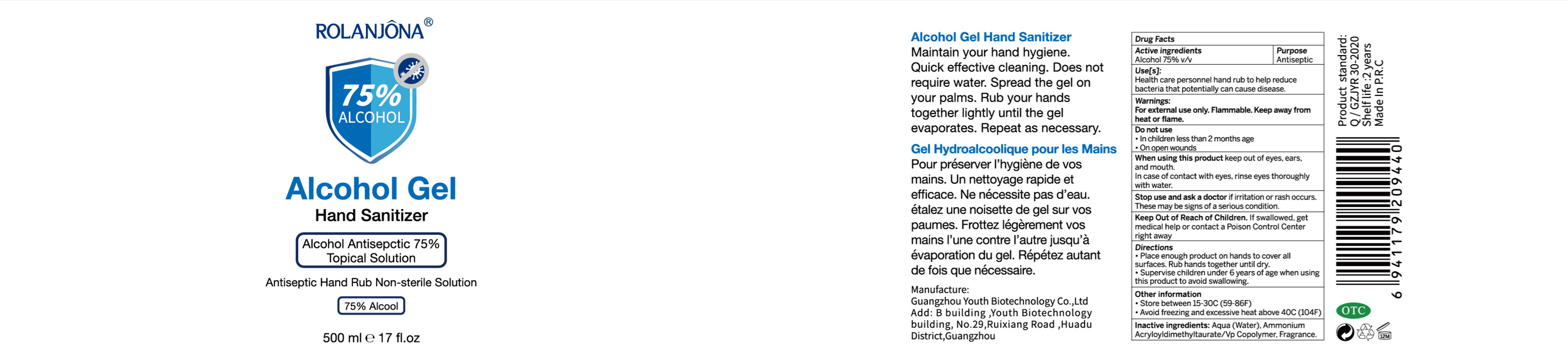 DRUG LABEL: HAND SANITIZER
NDC: 55879-002 | Form: LIQUID
Manufacturer: GUANGZHOU YOUTH BIOTECHNOLOGY CO., LTD
Category: otc | Type: HUMAN OTC DRUG LABEL
Date: 20200429

ACTIVE INGREDIENTS: ALCOHOL 375 mL/500 mL
INACTIVE INGREDIENTS: FRAGRANCE LAVENDER & CHIA F-153480; AMMONIUM ACRYLOYLDIMETHYLTAURATE/VP COPOLYMER; WATER

DOSAGE AND ADMINISTRATION

Store in a cool and ventilated place, .avoiding direct sunlight.

INACTIVE INGREDIENT

AMMONIUM ACRYLOYLDIMETHYLTAURATE/VP COPOLYMER

AQUA

FRAGRANCE

INDICATIONS AND USAGE

Take an appropriate amount and spread it on your hands evenly, and rub it until it is dry. .

ACTIVE INGREDIENT

ALCOHOL

keep out of reach of children

PURPOSE

Disinfection
Sterilization
No Rinseing

WARNINGS

1. For external use only, please do not take it internally. Please keep it out of reach of children.
2. Avoid contact with eyes. If get into your eyes,please. rinse with plenty of water and seek medical treatment in time.
3.Storage: Store in a cool and ventilated place,avoiding direct sunlight.